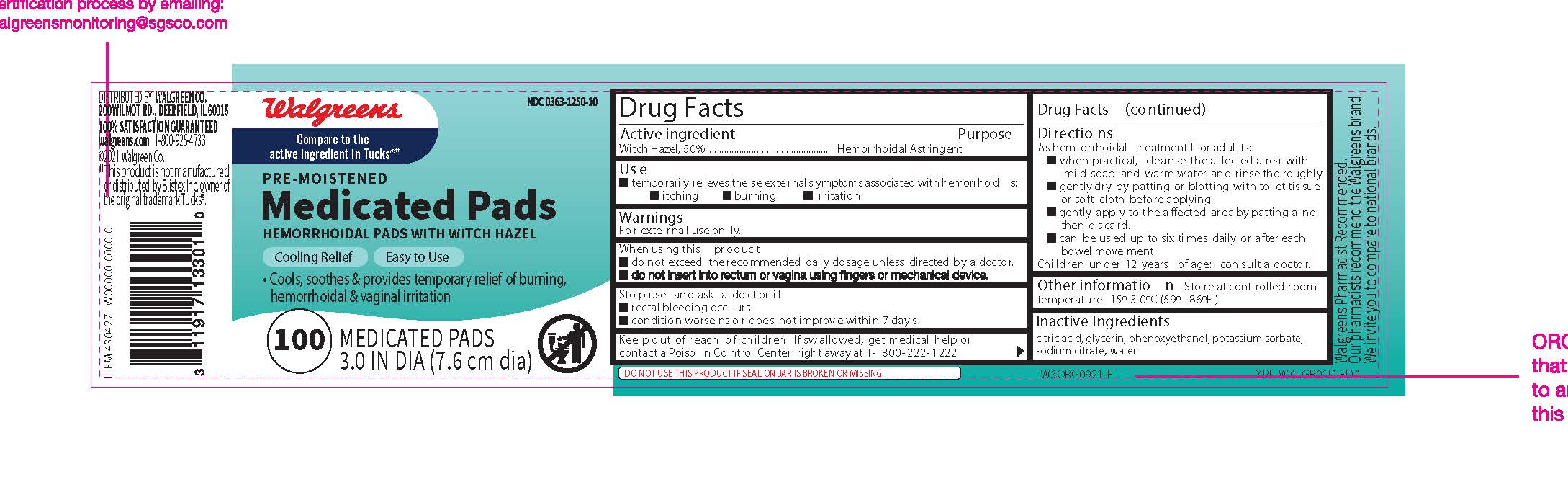 DRUG LABEL: Pre-moistened Medicated Pads, Pre-moistened Medicated Pads Hemorrhoidal Pads with Witch Hazel, Walgreens Pre-moistened Medicated Pads, Walgreens Pre-moistened Medicated Pads Hemorrhoidal Pads with Witch Hazel
NDC: 0363-1250 | Form: PATCH
Manufacturer: Walgreens Company
Category: otc | Type: HUMAN OTC DRUG LABEL
Date: 20250115

ACTIVE INGREDIENTS: WITCH HAZEL 50 mg/100 mg
INACTIVE INGREDIENTS: WATER; SODIUM CITRATE; ANHYDROUS CITRIC ACID; GLYCERIN; PHENOXYETHANOL; POTASSIUM SORBATE

Drug Facts

Active Ingredient

Witch Hazel, 50%

Purpose

Hemorrhoidal Astringent

Uses

Temporarily relieves these external symptoms associated with hemorrhoids:

- itching
- burning
- irritation

Warnings

For external use only.

When using this product

- do not exceed the recommended daily dosage unless directed by a doctor.
- do not insert into rectum or vagina using fingers or mechanical device.

Stop use and ask a doctor if

- rectal bleeding occurs
- condition worsens or does not improve within 7 days.

Keep out of reach of children.

If swallowed, get medical help or contact a Poison Control Center right away at 1-800-222-1222.

Directions

As hemorrhoidal treatment for adults:

- when practical, cleanse the affected area with mild soap and warm water and rinse thoroughly.
- gently dry by patting or blotting with toilet tissue or soft cloth before applying.
- gently apply to the affected area by patting and then discard.
- can be used up to six times daily or after each bowel movement.

Children under 12 years of age

- consult a doctor.

Other Information

Store at controlled room temperature: 15º-30ºC (59º-86ºF)

Inactive Ingredients

citric acid, glycerin, phenoxyethanol, potassium sorbate, sodium citrate, water

Principal Display Panel

NDC 0363-1250-10

Walgreens

Compare to the active ingredient in Tucks®††

Pre-Moistened Medicated Pads

HEMORRHOIDAL PADS WITH WITCH HAZEL

Cooling Relef

Easy to Use

Cools, soothes & provides temporary relief of burning, hemorrhoidal & vaginal irritation

100 Medicated Pads

3.0 IN DIA (7.6 cm dia)